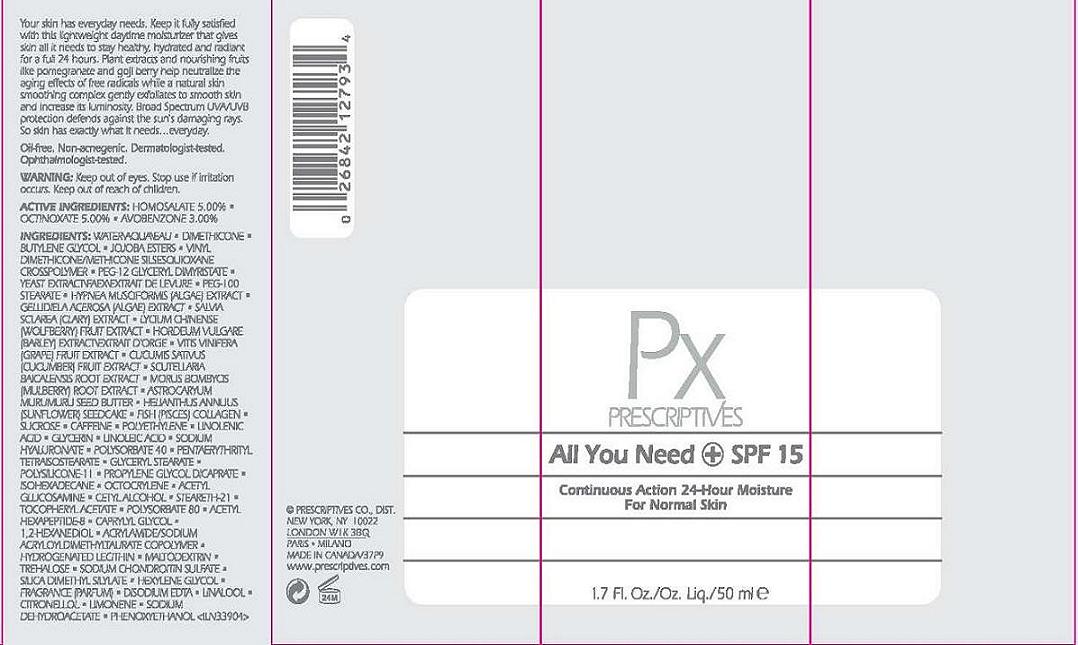 DRUG LABEL: ALL YOU NEED
NDC: 59158-719 | Form: LOTION
Manufacturer: PRESCRIPTIVES INC.
Category: otc | Type: HUMAN OTC DRUG LABEL
Date: 20110823

ACTIVE INGREDIENTS: HOMOSALATE 5.0 mL/100 mL; OCTINOXATE 5 mL/100 mL; AVOBENZONE 3 mL/100 mL
INACTIVE INGREDIENTS: WATER; DIMETHICONE; BUTYLENE GLYCOL; SIMMONDSIA CHINENSIS SEED WAX; PEG-12 GLYCERYL DIMYRISTATE; YEAST; PEG-100 STEARATE; HYPNEA MUSCIFORMIS; GELIDIELLA ACEROSA; CLARY SAGE; LYCIUM CHINENSIS FRUIT; BARLEY; WINE GRAPE; CUCUMBER; SCUTELLARIA BAICALENSIS ROOT; MORUS AUSTRALIS ROOT; ASTROCARYUM MURUMURU SEED BUTTER; HELIANTHUS ANNUUS SEEDCAKE; SUCROSE; CAFFEINE; LINOLENIC ACID; HYALURONATE SODIUM; POLYSORBATE 40; GLYCERYL MONOSTEARATE; PROPYLENE GLYCOL DICAPRATE; ISOHEXADECANE; N-ACETYLGLUCOSAMINE; CETYL ALCOHOL; STEARETH-21; ALPHA-TOCOPHEROL ACETATE; POLYSORBATE 80; ACETYL HEXAPEPTIDE-3; CAPRYLYL GLYCOL; 1,2-HEXANEDIOL; HYDROGENATED SOYBEAN LECITHIN; MALTODEXTRIN; TREHALOSE; HEXYLENE GLYCOL; EDETATE DISODIUM; SODIUM DEHYDROACETATE; PHENOXYETHANOL

ACTIVE INGREDIENT

ACTIVE INGREDIENTS: HOMOSALATE 5.00% [] OCTINOXATE 5.00% [] AVOBENZONE 3.00%

INACTIVE INGREDIENT

INACTIVE INGREDIENTS: WATER [] DIMETHICONE [] BUTYLENE GLYCOL [] JOJOBA ESTERS [] VINYL DIMETHICONE/METHICONE SILSESQUIOXANE CROSSPOLYMER [] PEG-12 GLYCERYL DIMYRISTATE [] YEAST EXTRACT\FAEX\EXTRAIT DE LEVURE [] PEG-100 STEARATE [] HYPNEA MUSCIFORMIS (ALGAE) EXTRACT [] GELLIDIELA ACEROSA (ALGAE) EXTRACT [] SALVIA SCLAREA (CLARY) EXTRACT [] LYCIUM CHINENSE (WOLFBERRY) FRUIT EXTRACT [] HORDEUM VULGARE (BARLEY) EXTRACT\EXTRAIT D'ORGE [] VITIS VINIFERA (GRAPE) FRUIT EXTRACT [] CUCUMIS SATIVUS (CUCUMBER) FRUIT EXTRACT [] SCUTELLARIA BAICALENSIS ROOT EXTRACT [] MORUS BOMBYCIS (MULBERRY) ROOT EXTRACT [] ASTROCARYUM MURUMURU SEED BUTTER [] HELIANTHUS ANNUUS (SUNFLOWER) SEEDCAKE [] FISH (PISCES) COLLAGEN [] SUCROSE [] CAFFEINE [] POLYETHYLENE [] LINOLENIC ACID [] GLYCERIN [] LINOLEIC ACID [] SODIUM HYALURONATE [] POLYSORBATE 40 [] PENTAERYTHRITYL TETRAISOSTEARATE [] GLYCERYL STEARATE [] POLYSILICONE-11 [] PROPYLENE GLYCOL DICAPRATE [] ISOHEXADECANE [] OCTOCRYLENE [] ACETYL GLUCOSAMINE [] CETYL ALCOHOL [] STEARETH-21 [] TOCOPHERYL ACETATE [] POLYSORBATE 80 [] ACETYL HEXAPEPTIDE-8 [] CAPRYLYL GLYCOL [] 1,2-HEXANEDIOL [] ACRYLAMIDE/SODIUM ACRYLOYLDIMETHYLTAURATE COPOLYMER [] HYDROGENATED LECITHIN [] MALTODEXTRIN [] TREHALOSE [] SODIUM CHONDROITIN SULFATE [] SILICA DIMETHYL SILYLATE [] HEXYLENE GLYCOL [] FRAGRANCE (PARFUM) [] DISODIUM EDTA [] LINALOOL [] CITRONELLOL [] LIMONENE [] SODIUM DEHYDROACETATE [] PHENOXYETHANOL

WARNINGS

WARNING: KEEP OUT OF EYES. STOP USE IF IRRITATION OCCURS. KEEP OUT OF REACH OF CHILDREN.

PACKAGE LABEL

PRINCIPAL DISPLAY PANEL:

PX
PRESCRIPTIVES
ALL YOU NEED + SPF 15
CONTINUOUS MOISTURE
24 HOUR MOISTURE FOR NORMAL SKIN
1.7 FL OZ/OZ LIQ/50 ML

PRESCRIPTIVES CO. DISTR
NEW YORK, NY 10022